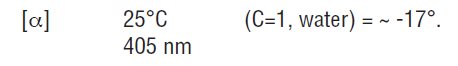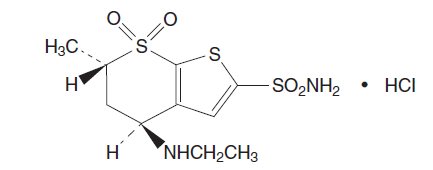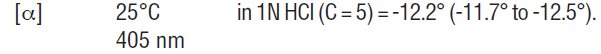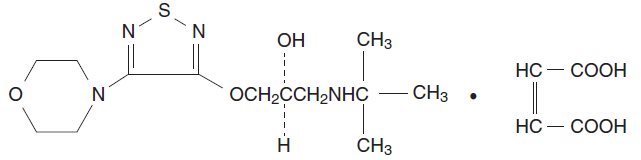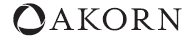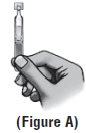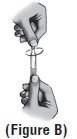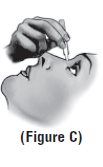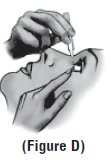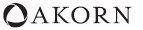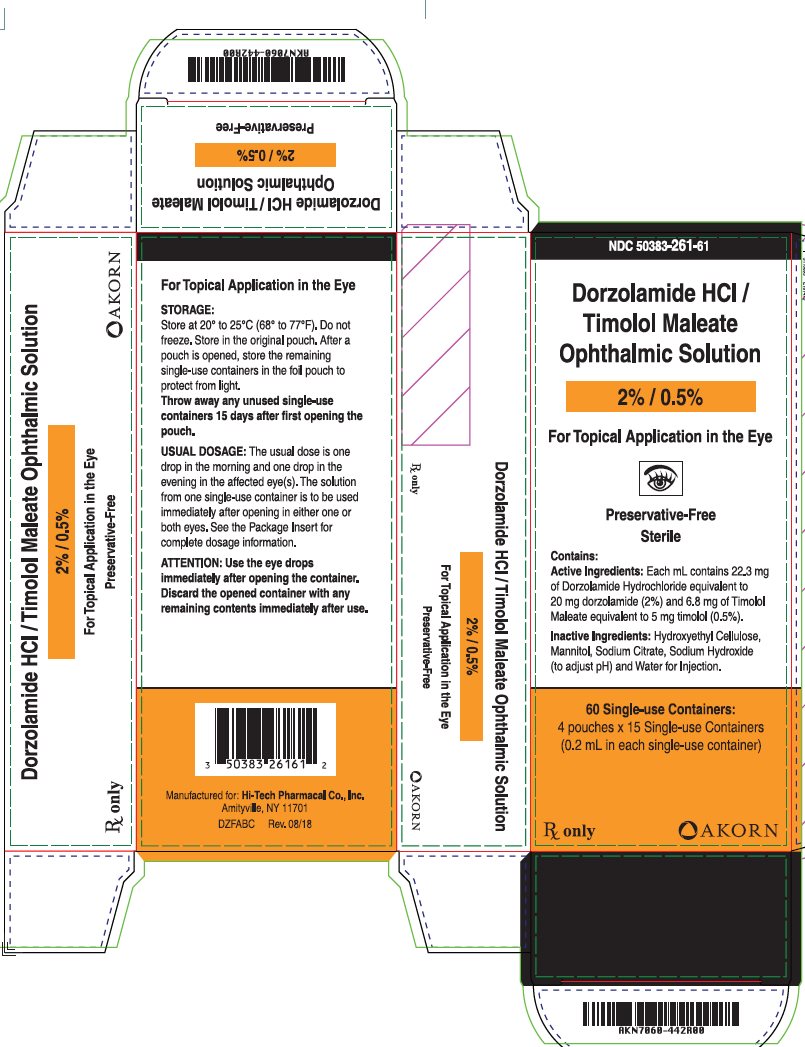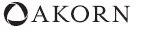 DRUG LABEL: Dorzolamide Hydrochloride and Timolol Maleate
NDC: 50383-261 | Form: SOLUTION/ DROPS
Manufacturer: Akorn
Category: prescription | Type: HUMAN PRESCRIPTION DRUG LABEL
Date: 20250910

ACTIVE INGREDIENTS: DORZOLAMIDE HYDROCHLORIDE 20 mg/1 mL; TIMOLOL MALEATE 5 mg/1 mL
INACTIVE INGREDIENTS: HYDROXYETHYL CELLULOSE (2000 MPA.S AT 1%); MANNITOL; SODIUM CITRATE, UNSPECIFIED FORM; SODIUM HYDROXIDE; WATER

HIGHLIGHTS OF PRESCRIBING INFORMATION

These highlights do not include all the information needed to use DORZOLAMIDE HYDROCHLORIDE-TIMOLOL MALEATE OPHTHALMIC SOLUTION (preservative-free) safely and effectively. See full prescribing information for DORZOLAMIDE HYDROCHLORIDE-TIMOLOL MALEATE OPHTHALMIC SOLUTION (preservative-free).
DORZOLAMIDE HYDROCHLORIDE-TIMOLOL MALEATE ophthalmic solution (preservative-free)
Initial U.S. Approval: 1998

1 INDICATIONS AND USAGE

- Dorzolamide hydrochloride-timolol maleate ophthalmic solution (preservative-free) is a carbonic anhydrase inhibitor with a beta-adrenergic receptor blocking agent indicated for the reduction of elevated intraocular pressure (IOP) in patients with open-angle glaucoma or ocular hypertension who are insufficiently responsive to beta-blockers.
- The IOP-lowering of dorzolamide hydrochloride-timolol maleate ophthalmic solution twice daily was slightly less than that seen with the concomitant administration of 0.5% timolol twice daily, and 2% dorzolamide three times daily. (1)

2 DOSAGE AND ADMINISTRATION

The dose is one drop of dorzolamide hydrochloride-timolol maleate ophthalmic solution (preservative-free) in the affected eye(s) two times daily. (2)

3 DOSAGE FORMS AND STRENGTHS

Solution containing 20 mg/mL dorzolamide and 5 mg/mL timolol. (3)

4 CONTRAINDICATIONS

Dorzolamide hydrochloride-timolol maleate ophthalmic solution (preservative-free) is contraindicated in patients with:

- Bronchial asthma or a history of bronchial asthma, severe chronic obstructive pulmonary disease. (4.1)
- Sinus bradycardia, second or third degree atrioventricular block, overt cardiac failure, cardiogenic shock. (4.2)
- Hypersensitivity to any component of this product. (4.3, 5.3)

5 WARNINGS AND PRECAUTIONS

- Potentiation of Respiratory Reactions Including Asthma (5.1)
- Cardiac Failure (5.2)
- Sulfonamide Hypersensitivity (5.3)
- Obstructive Pulmonary Disease (5.4)
- Increased Reactivity to Allergens (5.5)
- Potentiation of Muscle Weakness (5.6)
- Masking of Hypoglycemic Symptoms in Patients with Diabetes Mellitus (5.7)
- Masking of Thyrotoxicosis (5.8)
- Renal and Hepatic Impairment (5.9)
- Impairment of Beta-Adrenergically Mediated Reflexes During Surgery (5.10)

6 ADVERSE REACTIONS

The most frequently reported adverse reactions were taste perversion (bitter, sour, or unusual taste) or ocular burning and/or stinging in up to 30% of patients. Conjunctival hyperemia, blurred vision, superficial punctate keratitis or eye itching were reported between 5-15% of patients. (6)

To report SUSPECTED ADVERSE REACTIONS, contact Hi-Tech Pharmacal Co., Inc. at 1-800-262-9010 or FDA at 1-800-FDA-1088 or www.fda.gov/medwatch.

7 DRUG INTERACTIONS

- Potential additive effect of oral carbonic anhydrase inhibitor with dorzolamide hydrochloride-timolol maleate ophthalmic solution (preservative-free). (7.1)
- Potential acid-base and electrolyte disturbances. (7.2)
- Concomitant use with systemic beta-blockers may potentiate systemic beta-blockade. (7.3)
- Oral or intravenous calcium antagonists may cause atrioventricular conduction disturbances, left ventricular failure, and hypotension. (7.4)
- Catecholamine-depleting drugs may have additive effects and produce hypotension and/or marked bradycardia. (7.5)
- Digitalis and calcium antagonists may have additive effects in prolonging atrioventricular conduction time. (7.6)
- CYP2D6 inhibitors may potentiate systemic beta-blockade. (7.7)

FULL PRESCRIBING INFORMATION

1 INDICATIONS AND USAGE

Dorzolamide hydrochloride-timolol maleate ophthalmic solution (preservative-free) is indicated for the reduction of elevated intraocular pressure (IOP) in patients with open-angle glaucoma or ocular hypertension who are insufficiently responsive to beta-blockers (failed to achieve target IOP determined after multiple measurements over time). The IOP-lowering of dorzolamide hydrochloride-timolol maleate ophthalmic solution administered twice a day was slightly less than that seen with the concomitant administration of 0.5% timolol administered twice a day and 2% dorzolamide administered three times a day [see Clinical Studies (14.1)].

2 DOSAGE AND ADMINISTRATION

The dose is one drop of dorzolamide hydrochloride-timolol maleate ophthalmic solution (preservative-free) in the affected eye(s) two times daily.

If more than one topical ophthalmic drug is being used, the drugs should be administered at least five minutes apart [seeDrug Interactions (7.3)].

The solution from one individual unit is to be used immediately after opening for administration to one or both eyes. Since sterility cannot be maintained after the individual unit is opened, the remaining contents should be discarded immediately after administration.

3 DOSAGE FORMS AND STRENGTHS

Solution containing 20 mg/mL dorzolamide (22.26 mg of dorzolamide hydrochloride) and 5 mg/mL timolol (6.83 mg timolol maleate).

4 CONTRAINDICATIONS

4.1 Asthma, COPD

Dorzolamide hydrochloride-timolol maleate ophthalmic solution (preservative-free) is contraindicated in patients with bronchial asthma, a history of bronchial asthma, or severe chronic obstructive pulmonary disease [see Warnings and Precautions (5.1)].

4.2 Sinus Bradycardia, AV Block, Cardiac Failure, Cardiogenic Shock

Dorzolamide hydrochloride-timolol maleate ophthalmic solution (preservative-free) is contraindicated in patients with sinus bradycardia, second or third degree atrioventricular block, overt cardiac failure, and cardiogenic shock [seeWarnings and Precautions (5.2)].

4.3 Hypersensitivity

Dorzolamide hydrochloride-timolol maleate ophthalmic solution (preservative-free) is contraindicated in patients who are hypersensitive to any component of this product [see Warnings and Precautions (5.3)].

5 WARNINGS AND PRECAUTIONS

5.1 Potentiation of Respiratory Reactions Including Asthma

Dorzolamide hydrochloride-timolol maleate ophthalmic solution (preservative-free) contains timolol maleate, a beta-adrenergic blocking agent; and although administered topically, is absorbed systemically. Therefore, the same types of adverse reactions that are attributable to systemic administration of beta-adrenergic blocking agents may occur with topical administration. For example, severe respiratory reactions, including death due to bronchospasm in patients with asthma, and rarely death in association with cardiac failure, have been reported following systemic or ophthalmic administration of timolol maleate [see Contraindications (4.1) and Patient Counseling Information (17.1)].

5.2 Cardiac Failure

Sympathetic stimulation may be essential for support of the circulation in individuals with diminished myocardial contractility, and its inhibition by beta-adrenergic receptor blockade may precipitate more severe failure.

In patients without a history of cardiac failure continued depression of the myocardium with beta-blocking agents over a period of time can, in some cases, lead to cardiac failure. At the first sign or symptom of cardiac failure, dorzolamide hydrochloride-timolol maleate ophthalmic solution (preservative-free) should be discontinued [see Contraindications (4.2)and Patient Counseling Information (17.2)].

5.3 Sulfonamide Hypersensitivity

Dorzolamide hydrochloride-timolol maleate ophthalmic solution (preservativefree) contains dorzolamide, a sulfonamide; and although administered topically, it is absorbed systemically. Therefore, the same types of adverse reactions that are attributable to sulfonamides may occur with topical administration of dorzolamide hydrochloride-timolol maleate ophthalmic solution (preservative-free). Fatalities have occurred, although rarely, due to severe reactions to sulfonamides including Stevens-Johnson syndrome, toxic epidermal necrolysis, fulminant hepatic necrosis, agranulocytosis, aplastic anemia, and other blood dyscrasias. Sensitization may recur when a sulfonamide is readministered irrespective of the route of administration. If signs of serious reactions or hypersensitivity occur, discontinue the use of this preparation [seeContraindications (4.3) and Patient Counseling Information (17.3)].

5.4 Obstructive Pulmonary Disease

Patients with chronic obstructive pulmonary disease (e.g., chronic bronchitis, emphysema) of mild or moderate severity, bronchospastic disease, or a history of bronchospastic disease (other than bronchial asthma or a history of bronchial asthma, in which dorzolamide hydrochloride-timolol maleate ophthalmic solution (preservative-free) is contraindicated) should, in general, not receive beta-blocking agents, including dorzolamide hydrochloride-timolol maleate ophthalmic solution (preservative-free) [see Contraindications (4.1) and Patient Counseling Information (17.1)].

5.5 Increased Reactivity to Allergens

While taking beta-blockers, patients with a history of atopy or a history of severe anaphylactic reactions to a variety of allergens may be more reactive to repeated accidental, diagnostic, or therapeutic challenge with such allergens. Such patients may be unresponsive to the usual doses of epinephrine used to treat anaphylactic reactions.

5.6 Potentiation of Muscle Weakness

Beta-adrenergic blockade has been reported to potentiate muscle weakness consistent with certain myasthenic symptoms (e.g., diplopia, ptosis, and generalized weakness). Timolol has been reported rarely to increase muscle weakness in some patients with myasthenia gravis or myasthenic symptoms.

5.7 Masking of Hypoglycemic Symptoms in Patients with Diabetes Mellitus

Beta-adrenergic blocking agents should be administered with caution in patients subject to spontaneous hypoglycemia or to diabetic patients (especially those with labile diabetes) who are receiving insulin or oral hypoglycemic agents. Beta-adrenergic receptor blocking agents may mask the signs and symptoms of acute hypoglycemia.

5.8 Masking of Thyrotoxicosis

Beta-adrenergic blocking agents may mask certain clinical signs (e.g., tachycardia) of hyperthyroidism. Patients suspected of developing thyrotoxicosis should be managed carefully to avoid abrupt withdrawal of beta-adrenergic blocking agents that might precipitate a thyroid storm.

5.9 Renal and Hepatic Impairment

Dorzolamide has not been studied in patients with severe renal impairment (CrCl < 30 mL/min). Because dorzolamide and its metabolite are excreted predominantly by the kidney, dorzolamide hydrochloride-timolol maleate ophthalmic solution (preservative-free) is not recommended in such patients.

Dorzolamide has not been studied in patients with hepatic impairment and should therefore be used with caution in such patients.

5.10 Impairment of Beta-Adrenergically Mediated Reflexes During Surgery

The necessity or desirability of withdrawal of beta-adrenergic blocking agents prior to major surgery is controversial. Beta-adrenergic receptor blockade impairs the ability of the heart to respond to beta-adrenergically mediated reflex stimuli. This may augment the risk of general anesthesia in surgical procedures. Some patients receiving beta-adrenergic receptor blocking agents have experienced protracted severe hypotension during anesthesia. Difficulty in restarting and maintaining the heartbeat has also been reported. For these reasons, in patients undergoing elective surgery, some authorities recommend gradual withdrawal of beta-adrenergic receptor blocking agents.

If necessary during surgery, the effects of beta-adrenergic blocking agents may be reversed by sufficient doses of adrenergic agonists.

5.11 Corneal Endothelium

Carbonic anhydrase activity has been observed in both the cytoplasm and around the plasma membranes of the corneal endothelium. There is an increased potential for developing corneal edema in patients with low endothelial cell counts. Caution should be used when prescribing dorzolamide hydrochloride-timolol maleate ophthalmic solution (preservative-free) to this group of patients.

6 ADVERSE REACTIONS

6.1 Clinical Studies Experience

Because clinical trials are conducted under widely varying conditions, adverse reaction rates observed in the clinical trials of a drug cannot be directly compared to rates in the clinical trials of another drug and may not reflect the rates observed in practice.

Dorzolamide Hydrochloride-Timolol Maleate Ophthalmic Solution and Dorzolamide Hydrochloride-Timolol Maleate Ophthalmic Solution (Preservative-Free)

Dorzolamide hydrochloride-timolol maleate ophthalmic solution and dorzolamide hydrochloride-timolol maleate ophthalmic solution (preservative-free) were evaluated in patients with elevated intraocular pressure treated for open-angle glaucoma or ocular hypertension for up to 15 months. Approximately 5% of all patients discontinued therapy because of adverse reactions.

The most frequently reported adverse reactions occurring in up to 30% of patients were taste perversion (bitter, sour, or unusual taste) or ocular burning and/or stinging. The following adverse reactions were reported in 5-15% of patients: conjunctival hyperemia, blurred vision, superficial punctate keratitis or eye itching.

The following adverse reactions were reported in 1-5% of patients: abdominal pain, back pain, blepharitis, bronchitis, cloudy vision, conjunctival discharge, conjunctival edema, conjunctival follicles, conjunctival injection, conjunctivitis, corneal erosion, corneal staining, cortical lens opacity, cough, dizziness, dryness of eyes, dyspepsia, eye debris, eye discharge, eye pain, eye tearing, eyelid edema, eyelid erythema, eyelid exudate/scales, eyelid pain or discomfort, foreign body sensation, glaucomatous cupping, headache, hypertension, influenza, lens nucleus coloration, lens opacity, nausea, nuclear lens opacity, pharyngitis, post-subcapsular cataract, sinusitis, upper respiratory infection, urinary tract infection, visual field defect, vitreous detachment.

Other adverse reactions that have been reported with the individual components are listed below:

Dorzolamide 2%

Angioedema, asthenia/fatigue, bronchospasm, contact dermatitis, epistaxis, eyelid crusting, ocular discomfort, photophobia, signs and symptoms of ocular allergic reaction, transient myopia.

Timolol (ocular administration)

Body as a Whole: Asthenia/fatigue; Cardiovascular: Arrhythmia, syncope, cerebral ischemia, worsening of angina pectoris, palpitation, cardiac arrest, pulmonary edema, edema, claudication, Raynaud’s phenomenon, and cold hands and feet; Digestive: Anorexia; Immunologic: Systemic lupus erythematosus; Nervous System/Psychiatric: Increase in signs and symptoms of myasthenia gravis, somnolence, insomnia, nightmares, behavioral changes and psychic disturbances including confusion, hallucinations, anxiety, disorientation, nervousness, and memory loss; Skin: Alopecia, psoriasiform rash or exacerbation of psoriasis; Hypersensitivity: Signs and symptoms of systemic allergic reactions, including anaphylaxis, angioedema, urticaria, and localized and generalized rash; Respiratory: Bronchospasm (predominantly in patients with preexisting bronchospastic disease); Endocrine: Masked symptoms of hypoglycemia in diabetic patients; Special Senses: Ptosis, decreased corneal sensitivity, cystoid macular edema, visual disturbances including refractive changes and diplopia, pseudopemphigoid, and tinnitus; Urogenital: Retroperitoneal fibrosis, decreased libido, impotence, and Peyronie’s disease.

6.2 Post-Marketing Experience

The following adverse reactions have been identified during post-approval use of dorzolamide hydrochloride-timolol maleate ophthalmic solution or dorzolamide hydrochloride-timolol maleate ophthalmic solution (preservative-free). Because these reactions are reported voluntarily from a population of uncertain size, it is not always possible to reliably estimate their frequency or establish a causal relationship to drug exposure: bradycardia, cardiac failure, cerebral vascular accident, chest pain, choroidal detachment following filtration surgery, depression, diarrhea, dry mouth, dyspnea, heart block, hypotension, iridocyclitis, myocardial infarction, nasal congestion, Stevens-Johnson syndrome, toxic epidermal necrolysis, paresthesia, photophobia, respiratory failure, skin rashes, urolithiasis, and vomiting.

Timolol (oral administration)

The following additional adverse reactions have been reported in clinical experience with ORAL timolol maleate or other ORAL beta-blocking agents and may be considered potential effects of ophthalmic timolol maleate: Allergic: Erythematous rash, fever combined with aching and sore throat, laryngospasm with respiratory distress; Body as a Whole: Extremity pain, decreased exercise tolerance, weight loss; Cardiovascular: Worsening of arterial insufficiency, vasodilatation; Digestive: Gastrointestinal pain, hepatomegaly, mesenteric arterial thrombosis, ischemic colitis; Hematologic: Nonthrombocytopenic purpura; thrombocytopenic purpura, agranulocytosis; Endocrine: Hyperglycemia, hypoglycemia; Skin: Pruritus, skin irritation, increased pigmentation, sweating; Musculoskeletal: Arthralgia; Nervous System/Psychiatric: Vertigo, local weakness, diminished concentration, reversible mental depression progressing to catatonia, an acute reversible syndrome characterized by disorientation for time and place, emotional lability, slightly clouded sensorium, and decreased performance on neuropsychometrics; Respiratory: Rales, bronchial obstruction; Urogenital: Urination difficulties.

7 DRUG INTERACTIONS

7.1 Oral Carbonic Anhydrase Inhibitors

There is a potential for an additive effect on the known systemic effects of carbonic anhydrase inhibition in patients receiving an oral carbonic anhydrase inhibitor and dorzolamide hydrochloride-timolol maleate ophthalmic solution (preservative-free). The concomitant administration of dorzolamide hydrochloride-timolol maleate ophthalmic solution (preservative-free) and oral carbonic anhydrase inhibitors is not recommended.

7.2 High-Dose Salicylate Therapy

Although acid-base and electrolyte disturbances were not reported in the clinical trials with dorzolamide hydrochloride ophthalmic solution, these disturbances have been reported with oral carbonic anhydrase inhibitors and have, in some instances, resulted in drug interactions (e.g., toxicity associated with high-dose salicylate therapy). Therefore, the potential for such drug interactions should be considered in patients receiving dorzolamide hydrochloride-timolol maleate ophthalmic solution (preservative-free).

7.3 Beta-Adrenergic Blocking Agents

Patients who are receiving a beta-adrenergic blocking agent orally and dorzolamide hydrochloride-timolol maleate ophthalmic solution (preservativefree) should be observed for potential additive effects of beta-blockade, both systemic and on intraocular pressure. The concomitant use of two topical beta-adrenergic blocking agents is not recommended.

7.4 Calcium Antagonists

Caution should be used in the coadministration of beta-adrenergic blocking agents, such as dorzolamide hydrochloride-timolol maleate ophthalmic solution (preservative-free), and oral or intravenous calcium antagonists because of possible atrioventricular conduction disturbances, left ventricular failure, and hypotension. In patients with impaired cardiac function, coadministration should be avoided.

7.5 Catecholamine-Depleting Drugs

Close observation of the patient is recommended when a beta-blocker is administered to patients receiving catecholamine-depleting drugs such as reserpine, because of possible additive effects and the production of hypotension and/or marked bradycardia, which may result in vertigo, syncope, or postural hypotension.

7.6 Digitalis and Calcium Antagonists

The concomitant use of beta-adrenergic blocking agents with digitalis and calcium antagonists may have additive effects in prolonging atrioventricular conduction time.

7.7 CYP2D6 Inhibitors

Potentiated systemic beta-blockade (e.g., decreased heart rate, depression) has been reported during combined treatment with CYP2D6 inhibitors (e.g., quinidine, SSRIs) and timolol.

7.8 Clonidine

Oral beta-adrenergic blocking agents may exacerbate the rebound hypertension which can follow the withdrawal of clonidine. There have been no reports of exacerbation of rebound hypertension with ophthalmic timolol maleate.

8 USE IN SPECIFIC POPULATIONS

8.1 Pregnancy

Teratogenic Effects. Pregnancy Category C. Developmental toxicity studies with dorzolamide hydrochloride in rabbits at oral doses of ≥ 2.5 mg/kg/day (31 times the recommended human ophthalmic dose) revealed malformations of the vertebral bodies. These malformations occurred at doses that caused metabolic acidosis with decreased body weight gain in dams and decreased fetal weights. No treatment-related malformations were seen at 1 mg/kg/day (13 times the recommended human ophthalmic dose).

Teratogenicity studies with timolol in mice, rats, and rabbits at oral doses up to 50 mg/kg/day (7,000 times the systemic exposure following the maximum recommended human ophthalmic dose) demonstrated no evidence of fetal malformations. Although delayed fetal ossification was observed at this dose in rats, there were no adverse effects on postnatal development of offspring. Doses of 1,000 mg/kg/day (142,000 times the systemic exposure following the maximum recommended human ophthalmic dose) were maternotoxic in mice and resulted in an increased number of fetal resorptions. Increased fetal resorptions were also seen in rabbits at doses of 14,000 times the systemic exposure following the maximum recommended human ophthalmic dose, in this case without apparent maternotoxicity.

There are no adequate and well-controlled studies in pregnant women. Dorzolamide hydrochloride-timolol maleate ophthalmic solution (preservative-free) should be used during pregnancy only if the potential benefit justifies the potential risk to the fetus.

8.3 Nursing Mothers

It is not known whether dorzolamide is excreted in human milk. Timolol maleate has been detected in human milk following oral and ophthalmic drug administration. Because of the potential for serious adverse reactions from dorzolamide hydrochloride-timolol maleate ophthalmic solution (preservative-free) in nursing infants, a decision should be made whether to discontinue nursing or to discontinue the drug, taking into account the importance of the drug to the mother.

8.4 Pediatric Use

The safety and effectiveness of dorzolamide hydrochloride ophthalmic solution and timolol maleate ophthalmic solution have been established when administered individually in pediatric patients aged 2 years and older. Use of these drug products in these children is supported by evidence from adequate and well-controlled studies in children and adults. Safety and efficacy in pediatric patients below the age of 2 years have not been established.

8.5 Geriatric Use

No overall differences in safety or effectiveness have been observed between elderly and younger patients.

10 OVERDOSAGE

Symptoms consistent with systemic administration of beta-blockers or carbonic anhydrase inhibitors may occur, including electrolyte imbalance, development of an acidotic state, dizziness, headache, shortness of breath, bradycardia, bronchospasm, cardiac arrest and possible central nervous system effects. Serum electrolyte levels (particularly potassium) and blood pH levels should be monitored. [See Adverse Reactions (6).]

A study of patients with renal failure showed that timolol did not dialyze readily.

11 DESCRIPTION

Dorzolamide Hydrochloride-Timolol Maleate Ophthalmic Solution 2%/0.5% (Preservative-Free) is the combination of a topical carbonic anhydrase inhibitor and a topical beta-adrenergic receptor blocking agent.

Dorzolamide hydrochloride is described chemically as: (4S-trans)-4- (ethylamino)-5,6-dihydro-6-methyl-4H-thieno [2,3-b]thiopyran-2-sulfonamide 7,7-dioxide monohydrochloride. Dorzolamide hydrochloride is optically active. The specific rotation is:

Its empirical formula is C10H16N2O4S3•HCl and its structural formula is:

Dorzolamide hydrochloride has a molecular weight of 360.91. It is a white to off-white, crystalline powder, which is soluble in water and slightly soluble in methanol and ethanol.

Timolol maleate is described chemically as: (-)-1-(tert-butylamino)-3- [(4-morpholino-1,2,5-thiadiazol-3-yl)oxy]-2-propanol maleate (1:1) (salt). Timolol maleate possesses an asymmetric carbon atom in its structure and is provided as the levo-isomer. The optical rotation of timolol maleate is:

Its molecular formula is C13H24N4O3S•C4H4O4 and its structural formula is:

Timolol maleate has a molecular weight of 432.50. It is a white, odorless, crystalline powder which is soluble in water, methanol, and alcohol. Timolol maleate is stable at room temperature.

Dorzolamide Hydrochloride-Timolol Maleate Ophthalmic Solution 2%/0.5% (Preservative-Free) is supplied as a sterile, clear, colorless to nearly colorless, isotonic, buffered, slightly viscous, aqueous solution. The pH of the solution is approximately 5.65, and the osmolarity is 242-323 mOsM. Each mL of Dorzolamide Hydrochloride-Timolol Maleate Ophthalmic Solution 2%/0.5% (Preservative-Free) contains 20 mg dorzolamide (22.26 mg of dorzolamide hydrochloride) and 5 mg timolol (6.83 mg timolol maleate). Inactive ingredients are sodium citrate, hydroxyethyl cellulose, sodium hydroxide, mannitol, and water for injection.

Dorzolamide Hydrochloride-Timolol Maleate Ophthalmic Solution 2%/0.5% (Preservative-Free) does not contain a preservative.

12 CLINICAL PHARMACOLOGY

12.1 Mechanism of Action

Dorzolamide hydrochloride-timolol maleate ophthalmic solution (preservative-free) is comprised of two components: dorzolamide hydrochloride and timolol maleate. Each of these two components decreases elevated intraocular pressure, whether or not associated with glaucoma, by reducing aqueous humor secretion. Elevated intraocular pressure is a major risk factor in the pathogenesis of optic nerve damage and glaucomatous visual field loss. The higher the level of intraocular pressure, the greater the likelihood of glaucomatous field loss and optic nerve damage.

Dorzolamide hydrochloride is an inhibitor of human carbonic anhydrase II. Inhibition of carbonic anhydrase in the ciliary processes of the eye decreases aqueous humor secretion, presumably by slowing the formation of bicarbonate ions with subsequent reduction in sodium and fluid transport. Timolol maleate is a beta1 and beta2 (non-selective) adrenergic receptor blocking agent that does not have significant intrinsic sympathomimetic, direct myocardial depressant, or local anesthetic (membrane-stabilizing) activity. The combined effect of these two agents administered as dorzolamide hydrochloride-timolol maleate ophthalmic solution (preservative-free) administered twice daily results in additional intraocular pressure reduction compared to either component administered alone, but the reduction is not as much as when dorzolamide administered three times daily and timolol twice daily are administered concomitantly. [See Clinical Studies (14).]

12.3 Pharmacokinetics

Dorzolamide Hydrochloride

When topically applied, dorzolamide reaches the systemic circulation. To assess the potential for systemic carbonic anhydrase inhibition following topical administration, drug and metabolite concentrations in RBCs and plasma and carbonic anhydrase inhibition in RBCs were measured. Dorzolamide accumulates in RBCs during chronic dosing as a result of binding to CA-II. The parent drug forms a single N-desethyl metabolite, which inhibits CA-II less potently than the parent drug but also inhibits CA-I. The metabolite also accumulates in RBCs where it binds primarily to CA-I. Plasma concentrations of dorzolamide and metabolite are generally below the assay limit of quantitation (15 nM). Dorzolamide binds moderately to plasma proteins (approximately 33%).

Dorzolamide is primarily excreted unchanged in the urine; the metabolite also is excreted in urine. After dosing is stopped, dorzolamide washes out of RBCs nonlinearly, resulting in a rapid decline of drug concentration initially, followed by a slower elimination phase with a half-life of about four months.

To simulate the systemic exposure after long-term topical ocular administration, dorzolamide was given orally to eight healthy subjects for up to 20 weeks. The oral dose of 2 mg twice daily closely approximates the amount of drug delivered by topical ocular administration of dorzolamide 2% three times daily. Steady state was reached within 8 weeks. The inhibition of CA-II and total carbonic anhydrase activities was below the degree of inhibition anticipated to be necessary for a pharmacological effect on renal function and respiration in healthy individuals.

Timolol Maleate

In a study of plasma drug concentrations in six subjects, the systemic exposure to timolol was determined following twice daily topical administration of timolol maleate ophthalmic solution 0.5%. The mean peak plasma concentration following morning dosing was 0.46 ng/mL.

13 NONCLINICAL TOXICOLOGY

13.1 Carcinogenesis, Mutagenesis, Impairment of Fertility

In a two-year study of dorzolamide hydrochloride administered orally to male and female Sprague-Dawley rats, urinary bladder papillomas were seen in male rats in the highest dosage group of 20 mg/kg/day (250 times the recommended human ophthalmic dose). Papillomas were not seen in rats given oral doses equivalent to approximately 12 times the recommended human ophthalmic dose. No treatment-related tumors were seen in a 21- month study in female and male mice given oral doses up to 75 mg/kg/day (~900 times the recommended human ophthalmic dose).

The increased incidence of urinary bladder papillomas seen in the high-dose male rats is a class-effect of carbonic anhydrase inhibitors in rats. Rats are particularly prone to developing papillomas in response to foreign bodies, compounds causing crystalluria, and diverse sodium salts.

No changes in bladder urothelium were seen in dogs given oral dorzolamide hydrochloride for one year at 2 mg/kg/day (25 times the recommended human ophthalmic dose) or monkeys dosed topically to the eye at 0.4 mg/kg/day (~5 times the recommended human ophthalmic dose) for one year.

In a two-year study of timolol maleate administered orally to rats, there was a statistically significant increase in the incidence of adrenal pheochromocytomas in male rats administered 300 mg/kg/day (approximately 42,000 times the systemic exposure following the maximum recommended human ophthalmic dose). Similar differences were not observed in rats administered oral doses equivalent to approximately 14,000 times the maximum recommended human ophthalmic dose.

In a lifetime oral study of timolol maleate in mice, there were statistically significant increases in the incidence of benign and malignant pulmonary tumors, benign uterine polyps and mammary adenocarcinomas in female mice at 500 mg/kg/ day, (approximately 71,000 times the systemic exposure following the maximum recommended human ophthalmic dose), but not at 5 or 50 mg/kg/day (approximately 700 or 7,000, respectively, times the systemic exposure following the maximum recommended human ophthalmic dose). In a subsequent study in female mice, in which post-mortem examinations were limited to the uterus and the lungs, a statistically significant increase in the incidence of pulmonary tumors was again observed at 500 mg/kg/day.

The increased occurrence of mammary adenocarcinomas was associated with elevations in serum prolactin which occurred in female mice administered oral timolol at 500 mg/kg/day, but not at doses of 5 or 50 mg/kg/day. An increased incidence of mammary adenocarcinomas in rodents has been associated with administration of several other therapeutic agents that elevate serum prolactin, but no correlation between serum prolactin levels and mammary tumors has been established in humans. Furthermore, in adult human female subjects who received oral dosages of up to 60 mg of timolol maleate (the maximum recommended human oral dosage), there were no clinically meaningful changes in serum prolactin.

The following tests for mutagenic potential were negative for dorzolamide: (1) in vivo (mouse) cytogenetic assay; (2) invitro chromosomal aberration assay; (3) alkaline elution assay; (4) V-79 assay; and (5) Ames test.

Timolol maleate was devoid of mutagenic potential when tested in vivo (mouse) in the micronucleus test and cytogenetic assay (doses up to 800 mg/kg) and in vitro in a neoplastic cell transformation assay (up to 100 mg/mL). In Ames tests the highest concentrations of timolol employed, 5,000 or 10,000 mg/plate, were associated with statistically significant elevations of revertants observed with tester strain TA100 (in seven replicate assays), but not in the remaining three strains. In the assays with tester strain TA100, no consistent dose response relationship was observed, and the ratio of test to control revertants did not reach 2. A ratio of 2 is usually considered the criterion for a positive Ames test.

Reproduction and fertility studies in rats with either timolol maleate or dorzolamide hydrochloride demonstrated no adverse effect on male or female fertility at doses up to approximately 100 times the systemic exposure following the maximum recommended human ophthalmic dose.

14 CLINICAL STUDIES

14.1 Dorzolamide Hydrochloride-Timolol Maleate Ophthalmic Solution Efficacy

Clinical studies of 3 to 15 months duration were conducted to compare the IOP-lowering effect over the course of the day of dorzolamide hydrochloride-timolol maleate ophthalmic solution twice daily (dosed morning and bedtime) to individually- and concomitantly-administered 0.5% timolol twice daily and 2.0% dorzolamide twice and three times daily. The IOP-lowering effect of dorzolamide hydrochloride-timolol maleate ophthalmic solution twice daily was greater (1-3 mmHg) than that of monotherapy with either 2.0% dorzolamide three times daily or 0.5% timolol twice daily. The IOP-lowering effect of dorzolamide hydrochloride-timolol maleate ophthalmic solution twice daily was approximately 1 mmHg less than that of concomitant therapy with 2.0% dorzolamide three times daily and 0.5% timolol twice daily.

Open-label extensions of two studies were conducted for up to 12 months. During this period, the IOP-lowering effect of dorzolamide hydrochloride-timolol maleate ophthalmic solution twice daily was consistent during the 12 month follow-up period.

14.2 Dorzolamide Hydrochloride-Timolol Maleate Ophthalmic Solution (Preservative-Free) Equivalence Study

In an active-treatment controlled, parallel, double-masked study in 261 patients with elevated intraocular pressure ≥ 22 mmHg in one or both eyes, dorzolamide hydrochloride-timolol maleate ophthalmic solution (preservative-free) had an IOP-lowering effect equivalent to that of dorzolamide hydrochloride-timolol maleate ophthalmic solution.

16 HOW SUPPLIED/STORAGE AND HANDLING

Dorzolamide Hydrochloride-Timolol Maleate Ophthalmic Solution 2%/0.5% (Preservative-Free) is supplied in a foil pouch containing 15 low density polyethylene 0.2 mL single-use containers.

NDC 50383-261-61, package of 60 single-use vials in 4 pouches.

NDC 50383-261-91, package of 180 single-use vials in 12 pouches.

Store Dorzolamide Hydrochloride-Timolol Maleate Ophthalmic Solution 2%/0.5% (Preservative-Free) at 20° to 25°C (68° to 77°F). Do not freeze.

Store in the original pouch. After the pouch is opened, store the remaining single-use containers in the foil pouch to protect from light. Write down the date you open the foil pouch in the space provided on the pouch. Discard any unused containers 15 days after first opening the pouch.

17 PATIENT COUNSELING INFORMATION

See FDA-Approved Patient Labeling (Patient Information).

17.1 Potential for Exacerbation of Asthma and COPD

Dorzolamide hydrochloride-timolol maleate ophthalmic solution (preservative-free) may cause severe worsening of asthma and COPD symptoms including death due to bronchospasm. Patients with bronchial asthma, a history of bronchial asthma, severe chronic obstructive pulmonary disease should be advised not to take this product. [See Contraindications (4.1).]

17.2 Potential of Cardiovascular Effects

Dorzolamide hydrochloride-timolol maleate ophthalmic solution (preservative-free) may cause worsening of cardiac symptoms. Patients with sinus bradycardia, second or third degree atrioventricular block, or cardiac failure should be advised not to take this product. [See Contraindications (4.2).]

17.3 Sulfonamide Reactions

Dorzolamide hydrochloride-timolol maleate ophthalmic solution (preservative-free) contains dorzolamide (which is a sulfonamide) and, although administered topically, is absorbed systemically. Therefore the same types of adverse reactions that are attributable to sulfonamides may occur with topical administration, including severe skin reactions. Patients should be advised that if serious or unusual reactions or signs of hypersensitivity occur, they should discontinue the use of the product and seek their physician’s advice. [See Warnings and Precautions (5.3).]

17.4 Handling the Single-Use Container

Dorzolamide hydrochloride-timolol maleate ophthalmic solution (preservative-free) is a sterile solution that does not contain a preservative. The solution from one individual unit is to be used immediately after opening for administration to one or both eyes. Since sterility cannot be maintained after the individual unit is opened, the remaining contents should be discarded immediately after administration.

17.5 Intercurrent Ocular Conditions

Patients also should be advised that if they have ocular surgery or develop an intercurrent ocular condition (e.g., trauma or infection), they should immediately seek their physician’s advice concerning the continued use of this product.

17.6 Concomitant Topical Ocular Therapy

If more than one topical ophthalmic drug is being used, the drugs should be administered at least five minutes apart.

Manufactured for: Hi-Tech Pharmacal Co., Inc.

Amityville, NY 11701

DZF00N Rev. 08/18

AK60400

Patient Information

Dorzolamide Hydrochloride-Timolol Maleate

(dor-ZOLE-a-mide hye-droe-KLOHR-ide

TIM-uh-lawl MAL-ee-eyt)

Ophthalmic Solution 2%/0.5% (Preservative-Free)

Read this information before you start using dorzolamide hydrochloride-timolol maleate ophthalmic solution (preservative-free) and each time you get a refill. There may be new information. This information does not take the place of talking to your doctor about your medical condition or your treatment.

What is dorzolamide hydrochloride-timolol maleate ophthalmic solution (preservative-free)?

Dorzolamide hydrochloride-timolol maleate ophthalmic solution (preservative-free) is a prescription sterile eye drop solution that contains 2 medicines, dorzolamide hydrochloride (a sulfonamide carbonic anhydrase inhibitor) and timolol maleate (a beta-adrenergic blocker). Dorzolamide hydrochloride-timolol maleate ophthalmic solution (preservative-free) is used to lower the pressure in the eye (intraocular pressure) in people with open-angle glaucoma or ocular hypertension, when their eye pressure is too high and beta-adrenergic blocker medicines alone have not adequately lowered the pressure.

It is not known if dorzolamide hydrochloride-timolol maleate ophthalmic solution (preservative-free) is safe and effective in children under 2 years of age.

Who should not use dorzolamide hydrochloride-timolol maleate ophthalmic solution (preservative-free)?

Do not use dorzolamide hydrochloride-timolol maleate ophthalmic solution (preservative-free) if you:

- have or have had asthma
- have or have had severe lung problems (chronic obstructive pulmonary disease)
- have heart problems, including slow or irregular heartbeat or heart failure
- are allergic to dorzolamide hydrochloride, timolol maleate, or any of the ingredients in dorzolamide hydrochloride-timolol maleate ophthalmic solution (preservative-free).

Talk to your healthcare provider before taking this medicine if you have any of these conditions.

What should I tell my doctor before using dorzolamide hydrochloride-timolol maleate ophthalmic solution (preservative-free)?

Before you use dorzolamide hydrochloride-timolol maleate ophthalmic solution (preservative-free), tell your doctor if you:

- have problems with muscle weakness (myasthenia gravis)
- have diabetes or problems with low blood sugar (hypoglycemia)
- have thyroid, kidney, or liver problems
- are planning to have surgery
- are allergic to sulfa drugs
- have or have had eye problems, including any surgery on your eye or eyes, or are using any other eye medicines
- have any other medical problems
- are pregnant or plan to become pregnant. It is not known if dorzolamide hydrochloride-timolol maleate ophthalmic solution (preservative-free) will harm your unborn baby. If you become pregnant while using dorzolamide hydrochloride-timolol maleate ophthalmic solution (preservative-free) talk to your doctor right away.
- are breastfeeding or plan to breastfeed. It is not known whether dorzolamide passes into your
breast milk however, timolol has been detected in breast milk. Talk to your doctor about the best
way to feed your baby if you use dorzolamide hydrochloride-timolol maleate ophthalmic solution
(preservative-free).
Tell your doctor about all the medicines you take, including prescription and non-prescription medicines,
vitamins, and herbal supplements.
Dorzolamide hydrochloride-timolol maleate ophthalmic solution (preservative-free) and other medicines may affect each other causing side effects. Dorzolamide hydrochloride-timolol maleate ophthalmic solution (preservative-free) may affect the way other medicines work, and other medicines may affect how dorzolamide hydrochloride-timolol maleate ophthalmic solution (preservative-free) works.
Know the medicines you take. Keep a list of them to show your doctor and pharmacist when you get a new medicine.
How should I use dorzolamide hydrochloride-timolol maleate ophthalmic solution (preservative-free)?
Read the Instructions for Use at the end of this Patient Information leaflet for additional instructions about the right way to use dorzolamide hydrochloride-timolol maleate ophthalmic solution (preservative-free).

What are the possible side effects of dorzolamide hydrochloride-timolol maleate ophthalmic solution (preservative-free)?

Dorzolamide hydrochloride-timolol maleate ophthalmic solution (preservative-free) may cause serious side effects including:

- severe breathing problems. These breathing problems can happen in people who have asthma, chronic obstructive pulmonary disease, or heart failure and can cause death. Tell your doctor right away if you have breathing problems while taking dorzolamide hydrochloride-timolol maleate ophthalmic solution (preservative-free).
- heart failure. This can happen in people who already have heart failure and in people who have never had heart failure before. Tell your doctor right away if you get any of these symptoms of heart failure while taking dorzolamide hydrochloride-timolol maleate ophthalmic solution (preservative-free):
- shortness of breath
- irregular heartbeat (palpitations)
- swelling of your ankles or feet
- sudden weight gain
- severe allergic reactions. These allergic reactions can happen the first time you use dorzolamide hydrochloride-timolol maleate ophthalmic solution (preservative-free) or after you have been using dorzolamide hydrochloride-timolol maleate ophthalmic solution (preservative-free) for a while and may cause death. Stop taking dorzolamide hydrochloride-timolol maleate ophthalmic solution (preservative-free) and call your doctor right away or get emergency help if you get any of these symptoms of an allergic reaction
- swelling of your face, lips, mouth, or tongue
- trouble breathing
- wheezing
- severe itching
- skin rash, redness, or swelling
- dizziness or fainting
- fast heartbeat or pounding in your chest (tachycardia)
- sweating
- worsening muscle weakness. Dorzolamide hydrochloride-timolol maleate ophthalmic solution (preservative-free) can cause muscle weakness to get worse in people who already have problems with muscle weakness (myasthenia gravis).
- kidney problems. Your doctor may do tests to check your kidney function while you use dorzolamide hydrochloride-timolol maleate ophthalmic solution (preservative-free).
- swelling of your eye (cornea)

The most common side effects of dorzolamide hydrochloride-timolol maleate ophthalmic solution (preservative-free) include:

- a bitter, sour, or unusual taste in your mouth after using dorzolamide hydrochloride-timolol maleate ophthalmic solution (preservative-free)
- burning, stinging, redness, or itching of the eye
- blurred vision
- painful, red, watery eyes with increased sensitivity (superficial punctate keratitis)

Tell your doctor if you have any new eye problems while using dorzolamide hydrochloride-timolol maleate ophthalmic solution (preservative-free) including:

- an eye injury
- an eye infection
- a sudden loss of vision
- eye surgery
- swelling and redness of and around your eye (conjunctivitis)
- problems with your eyelids

Tell your doctor if you have any other side effects that bother you.

These are not all the possible side effects of dorzolamide hydrochloride-timolol maleate ophthalmic solution (preservative-free). For more information, ask your doctor or pharmacist.

Call your doctor about medical advice about side effects. You may report side effects to FDA at 1-800-FDA-1088.

What should I do in case of an overdose?

If you swallow the contents of the container, contact your doctor immediately. Among other effects, you may feel light-headed, have difficulty breathing, or feel your heart rate has slowed.

How should I store dorzolamide hydrochloride-timolol maleate ophthalmic solution (preservative-free)?

- Store dorzolamide hydrochloride-timolol maleate ophthalmic solution (preservative-free) at room temperature between 68°F to 77°F (20°C to 25°C). Do not freeze.
- Keep the dorzolamide hydrochloride-timolol maleate ophthalmic solution (preservative-free) single-use containers in their original foil pouch to protect from light.
- Write down the date you open the foil pouch in the space provided on the pouch.
- Throw away all unused dorzolamide hydrochloride-timolol maleate ophthalmic solution (preservative-free) single-use containers 15 days after first opening the pouch.

Keep dorzolamide hydrochloride-timolol maleate ophthalmic solution (preservative-free) and all medicines out of the reach of children.

General information about the safe and effective use of dorzolamide hydrochloride-timolol maleate ophthalmic solution (preservative-free).

Medicines are sometimes prescribed for purposes other than those listed in a Patient Information leaflet. Do not use dorzolamide hydrochloride-timolol maleate ophthalmic solution (preservative-free) for a condition for which it was not prescribed. Do not give dorzolamide hydrochloride-timolol maleate ophthalmic solution (preservative-free) to other people, even if they have the same symptoms you have. It may harm them. This Patient Information leaflet summarizes the most important information about dorzolamide hydrochloridetimolol maleate ophthalmic solution (preservative-free). If you would like more information, talk with your doctor. You can ask your pharmacist or doctor for information about dorzolamide hydrochloride-timolol maleate ophthalmic solution (preservative-free) that is written for health professionals.

What are the ingredients in dorzolamide hydrochloride-timolol maleate ophthalmic solution (preservative-free)?

Active ingredients: dorzolamide hydrochloride and timolol maleate

Inactive ingredients: sodium citrate, hydroxyethyl cellulose, sodium hydroxide, mannitol, and water for injection.

Instructions for Use

Read these instructions before using your dorzolamide hydrochloride-timolol maleate ophthalmic solution (preservative-free) and each time you get a refill. There may be new information. This leaflet does not take the place of talking with your doctor about your medical condition or your treatment.

Important:

- Dorzolamide hydrochloride-timolol maleate ophthalmic solution (preservative-free) is for the eye only. Do not swallow dorzolamide hydrochloride-timolol maleate ophthalmic solution (preservative-free).
- Dorzolamide hydrochloride-timolol maleate ophthalmic solution (preservative-free) single-use containers are packaged in a foil pouch.
- Write down the date you open the foil pouch in the space provided on the pouch.

Every time you use dorzolamide hydrochloride-timolol maleate ophthalmic solution (preservative-free):

Step 1. Wash your hands.

Step 2. Take the strip of single-use containers from the pouch.

Step 3. Pull off 1 single-use container from the strip.

Step 4. Put the remaining strip of single-use containers back in the pouch and fold the edge to close the pouch.

Step 5. Hold the single-use container upright. Make sure

that the solution is in the bottom part of the single-

use container (See Figure A).

Step 6. Open the single-use container by twisting off the

tab (See Figure B).

Step 7. Tilt your head backwards. If you are unable to tilt

your head, lie down.

Step 8. Place the tip of the single-use container close to

your eye. Be careful not to touch your eye with

the tip of the single-use container (See Figure C).

Step 9. Pull the lower eyelid downwards and look up.

Step 10. Gently squeeze the container and let 1 drop of

Dorzolamide hydrochloride-timolol maleate

ophthalmic solution (preservative-free) fall into

the space between your lower eyelid and your

eye. If a drop misses your eye, try again (See

Figure D).

Step 11. Blot any excess solution from the skin around the eye with a tissue.

- If your doctor has told you to use drops in both eyes, repeat steps 7 to 11 for your other eye.
- There is enough dorzolamide hydrochloride-timolol maleate ophthalmic solution (preservative-free) in 1 single-use container for 1 or both of your eyes.
- Throw away the opened single-use container with any remaining dorzolamide hydrochloride-timolol maleate ophthalmic solution (preservative-free) right away.

This Patient Information and Instructions for Use have been approved by the U.S. Food and Drug Administration.

Manufactured for: Hi-Tech Pharmacal Co., Inc.

Amityville, NY 11701

DZFA0N Rev. 08/18

AK60400

PACKAGE/LABEL PRINCIPAL DISPLAY PANEL

NDC 50383-261-61

Dorzalamide HCl/Timolol Maleate Ophthalmic Solution

2%/5%

For Topical Application in the Eyes

Preservative-Free

Sterile

Contains:

Active Ingredients: Each mL contains 22.3 mg of Dorzolamide Hydrochloride equivalent to 20 mg dorzolamide (2%) and 6.8 mg of Timolol Maleate equivalent to 5 mg timolol (0.5%).

Inactive Ingredients: Hydroxyethyl Cellulose, Mannitol, Sodium Citrate, Sodium Hydroxide (to adjust pH) and Water for injection.

60 Single-use Containers:

4 pouches x 15 Single-use Containers

(0.2 mL in each single-use container)

Rx only